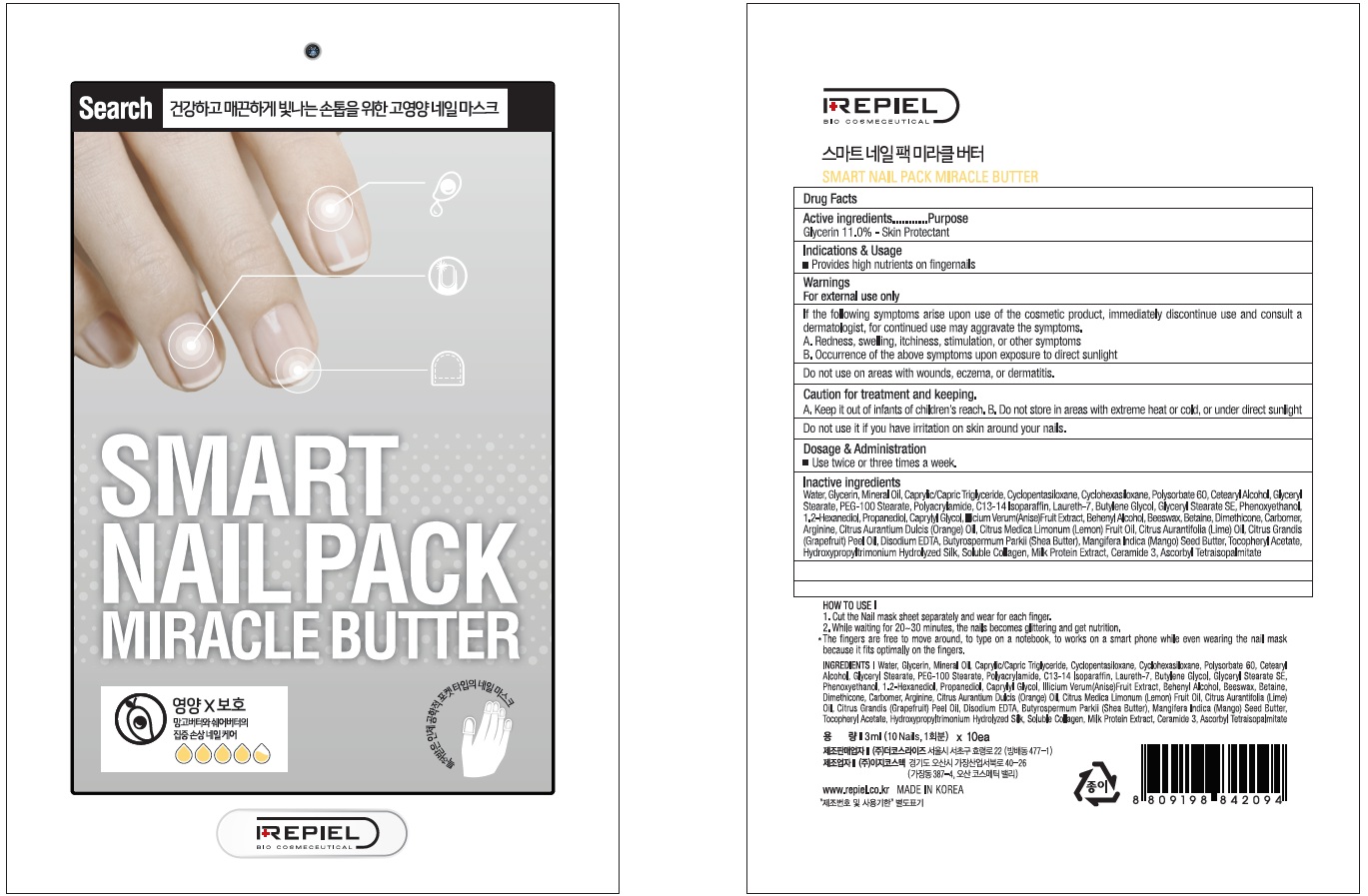 DRUG LABEL: REPIEL SMART NAIL PACK MIRACLE BUTTER
NDC: 70758-020 | Form: PATCH
Manufacturer: THE COSRISE CO.,LTD
Category: otc | Type: HUMAN OTC DRUG LABEL
Date: 20160629

ACTIVE INGREDIENTS: Glycerin 0.33 g/3 mL
INACTIVE INGREDIENTS: Water; Mineral Oil

ACTIVE INGREDIENT

Active Ingredient: Glycerin 11.0%

INACTIVE INGREDIENT

Inactive Ingredients: Water, Mineral Oil, Caprylic/Capric Triglyceride, Cyclopentasiloxane, Cyclohexasiloxane, Polysorbate 60, Cetearyl Alcohol, Glyceryl Stearate, PEG-100 Stearate, Polyacrylamide, C13-14 Isoparaffin, Laureth-7, Butylene Glycol, Glyceryl Stearate SE, Phenoxyethanol, 1.2-Hexanediol, Propanediol, Caprylyl Glycol, Illicium Verum(Anise)Fruit Extract, Behenyl Alcohol, Beeswax, Betaine, Dimethicone, Carbomer, Arginine, Citrus Aurantium Dulcis (Orange) Oil, Citrus Medica Limonum (Lemon) Fruit Oil, Citrus Aurantifolia (Lime) Oil, Citrus Grandis (Grapefruit) Peel Oil, Disodium EDTA, Butyrospermum Parkii (Shea Butter), Mangifera Indica (Mango) Seed Butter, Tocopheryl Acetate, Hydroxypropyltrimonium Hydrolyzed Silk, Soluble Collagen, Milk Protein Extract, Ceramide 3, Ascorbyl Tetraisopalmitate

PURPOSE

Purpose: Skin Protectant

WARNINGS

Warnings: For external use only 1. If the following symptoms arise upon use of the cosmetic product, immediately discontinue use and consult a dermatologist, for continued use may aggravate the symptoms. A. Redness, swelling, itchiness, stimulation, or other symptoms B. Occurrence of the above symptoms upon exposure to direct sunlight. 2. Do not use on areas with wounds, eczema, or dermatitis. 3. Caution for treatment and keeping. A. Keep it out of infants of children's reach. B. Do not store in areas with extreme heat or cold, or under direct sunlight. 4. Do not use it if you have irritation on skin around your nails.

KEEP OUT OF REACH OF CHILDREN

Keep it out of infants of children's reach.

INDICATIONS & USAGE

Indications & Usage: Provides high nutrients on fingernails

How to use: 1. Cut the Nail mask sheet separately and wear for each finger. 2. While waiting for 20~30 minutes, the nails becomes glittering and get nutrition. (The fingers are free to move around, to type on notebook, to works on a smart phone while even wearing the nail mask because it fits optimally on the fingers.)

DOSAGE & ADMINISTRATION

Dosage & Administration: Use twice or three times a week.